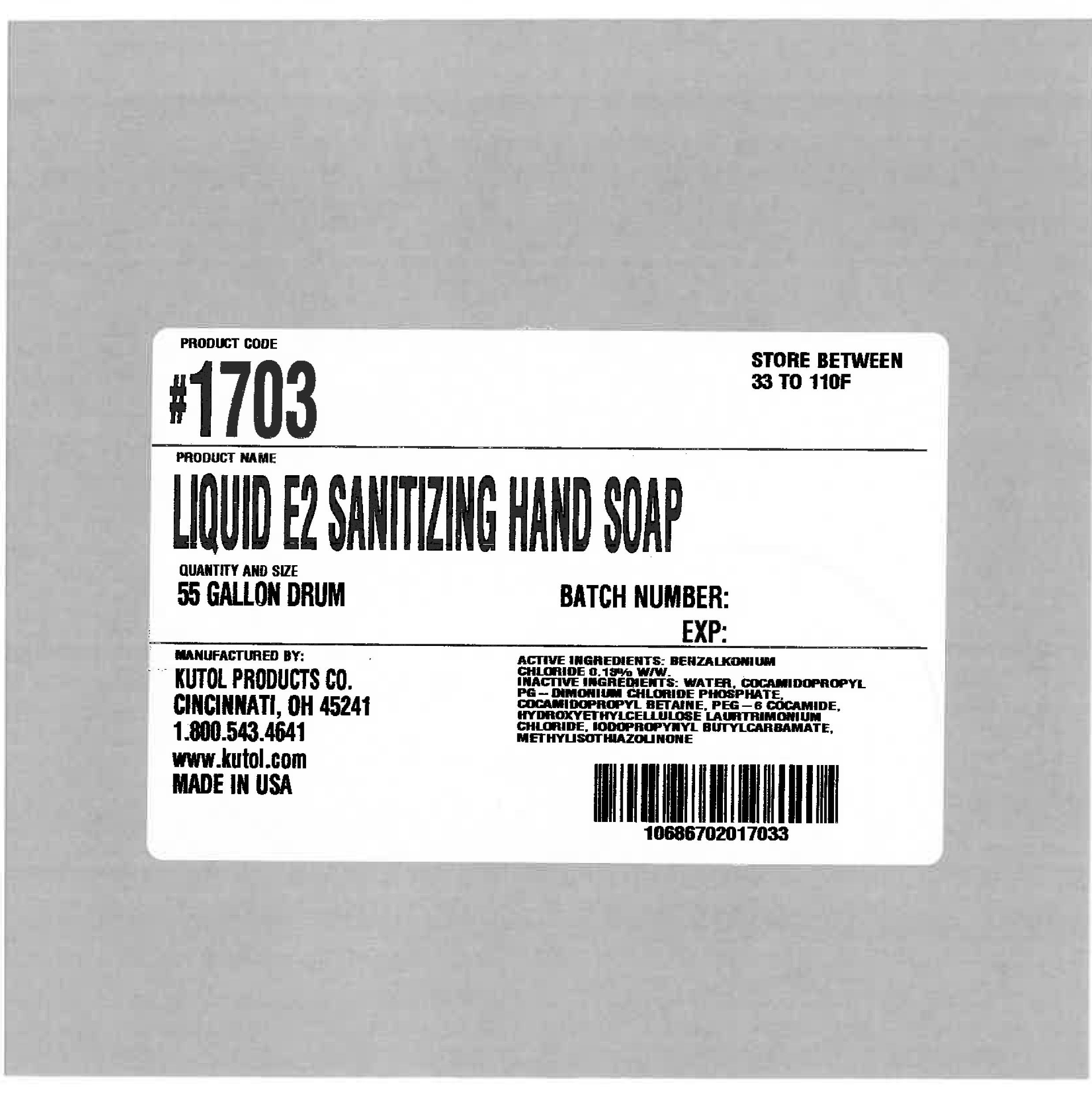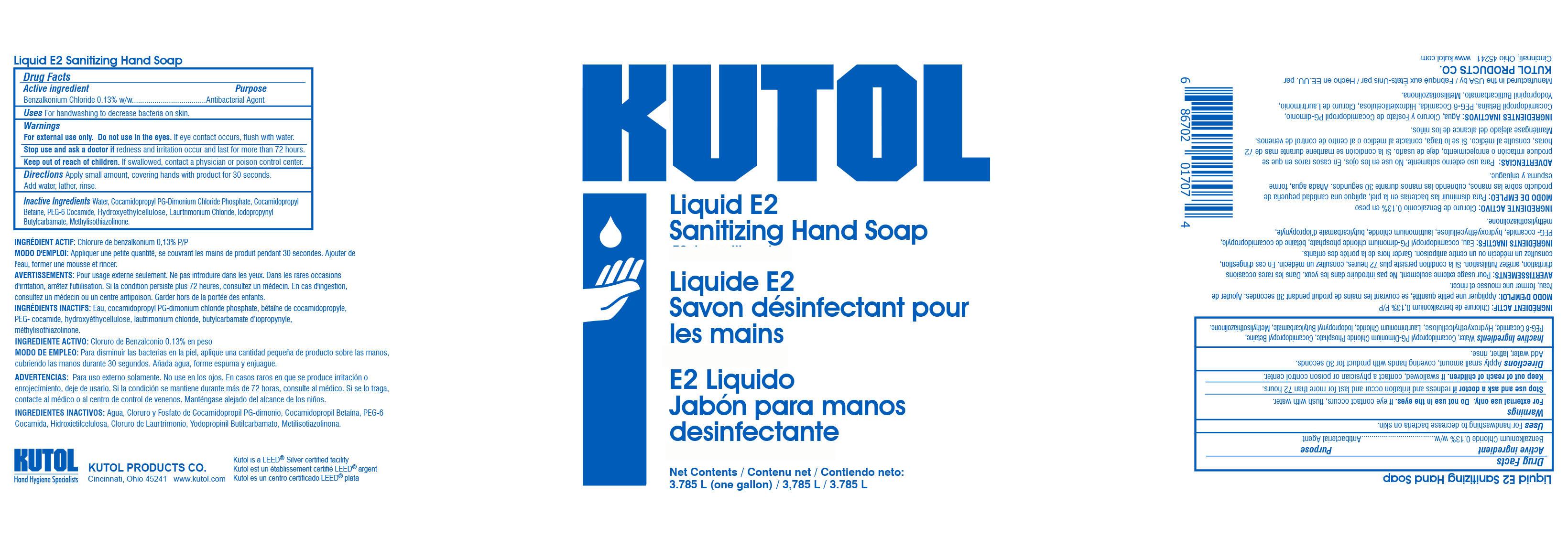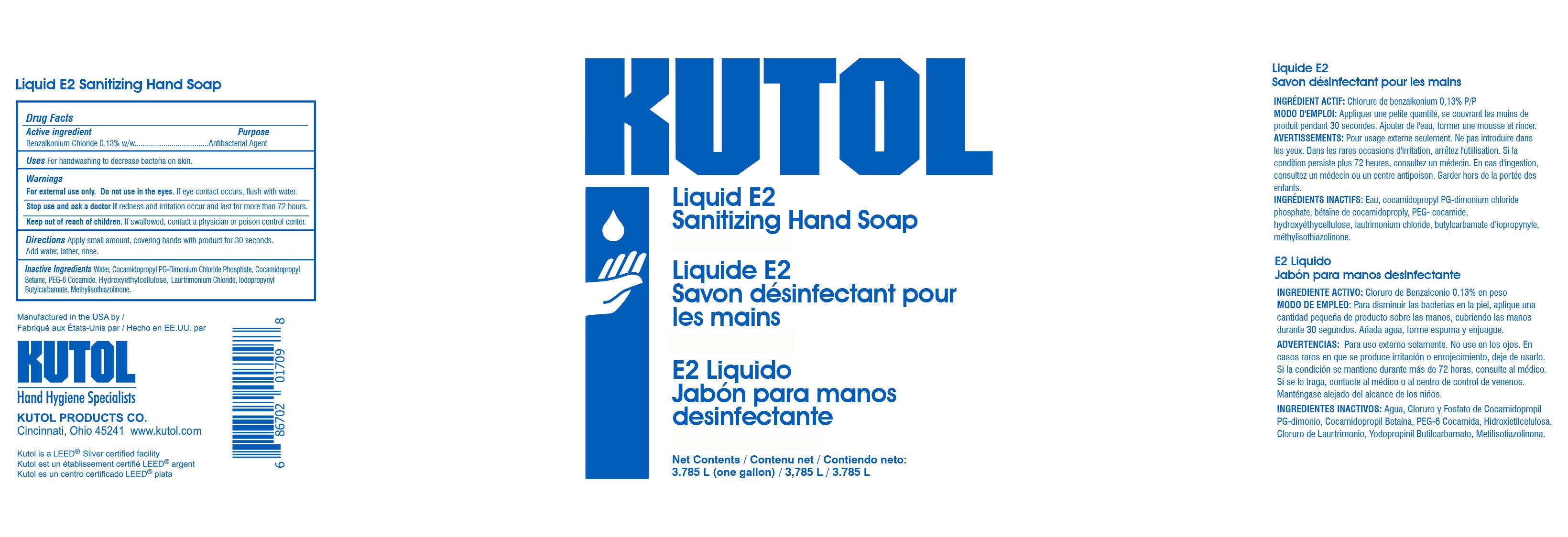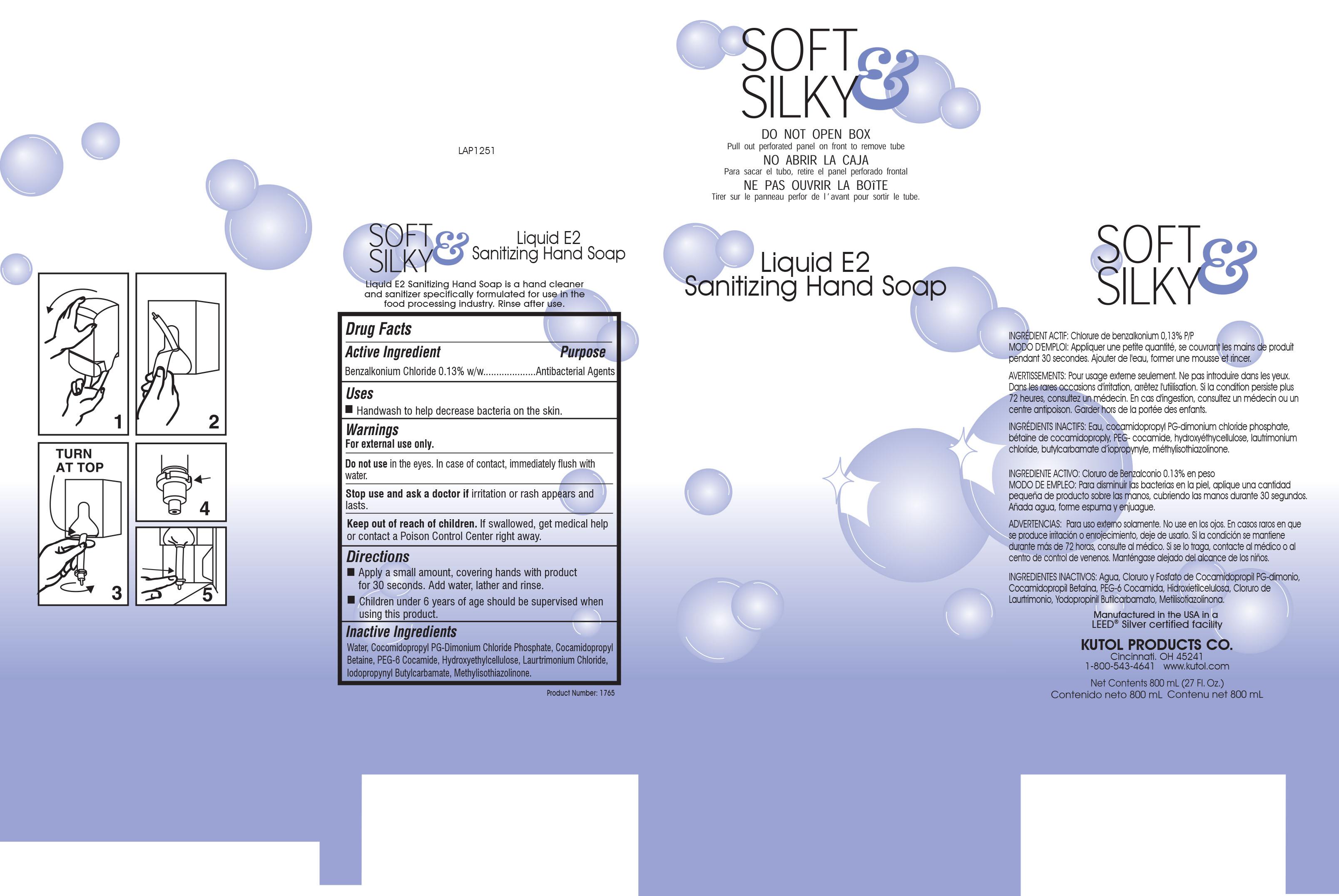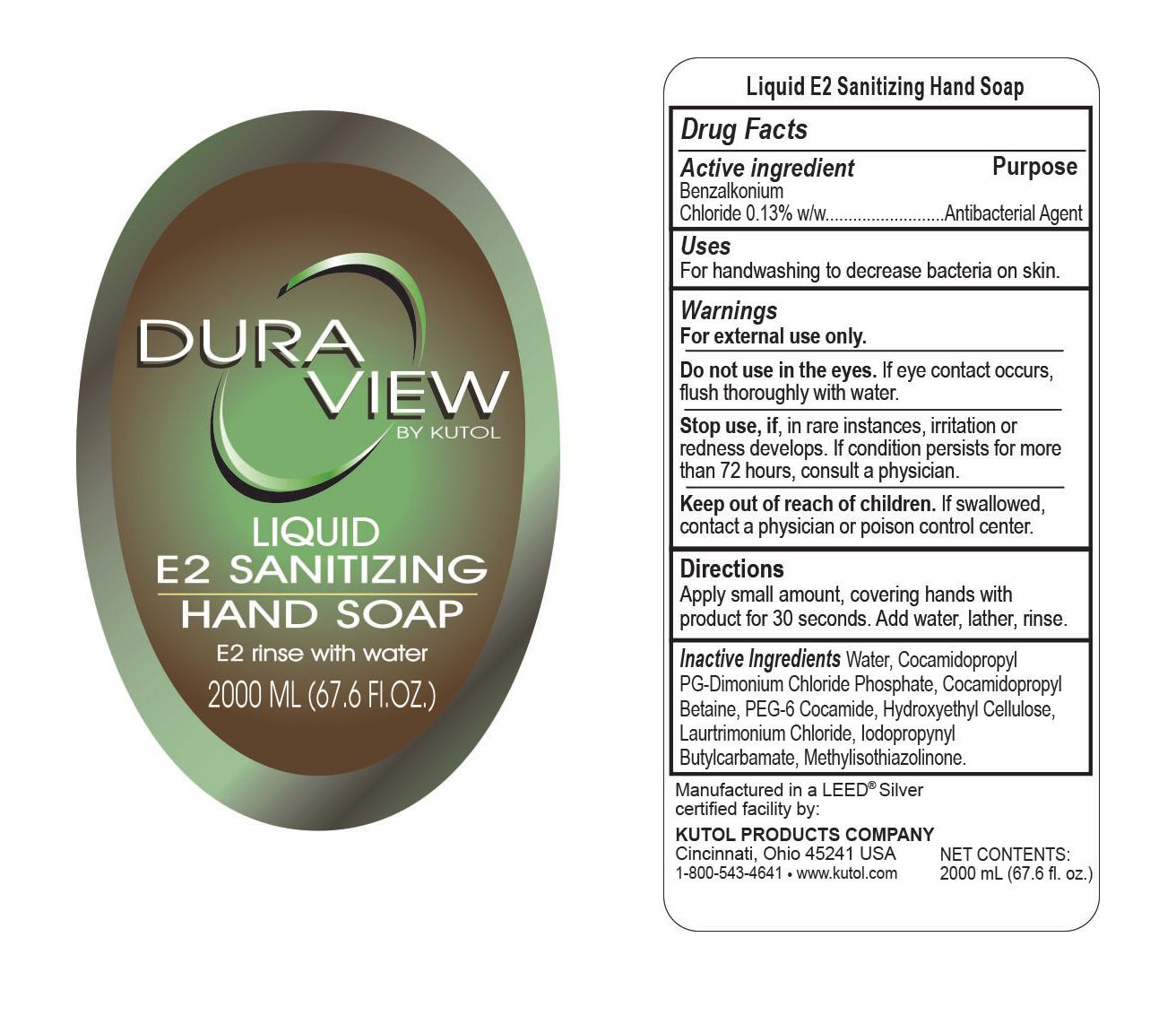 DRUG LABEL: E2 SANITIZING HAND
NDC: 50865-017 | Form: SOAP
Manufacturer: KUTOL PRODUCTS COMPANY
Category: otc | Type: HUMAN OTC DRUG LABEL
Date: 20241218

ACTIVE INGREDIENTS: BENZALKONIUM CHLORIDE 0.003 mg/1 mL
INACTIVE INGREDIENTS: WATER; COCAMIDOPROPYL BETAINE; COCAMIDOPROPYL PG-DIMONIUM CHLORIDE PHOSPHATE; PEG-6 COCAMIDE; HYDROXYETHYL CELLULOSE (280 MPA.S AT 2%); LAURTRIMONIUM CHLORIDE; METHYLISOTHIAZOLINONE; IODOPROPYNYL BUTYLCARBAMATE

F017 LIQUID E2 SANITIZING HAND SOAP

Active Ingredient

Benzalkonium Chloride 0.13% w/w

Purpose

Antibacterial Agent

Uses

For handwashing to help reduce bacteria on the skin that could cause disease.

Warnings

For external use only. Avoid contact with eyes. If contact occurs, flush with water.

Stop use and ask a doctor if, in rare instances, redness or irritation develops and persists for more than 72 hours.

Keep out of reach of children. If swallowed, contact a physician or poison control center.

Directions

To decrease bacteria on skin, apply small amount, covering hands with product for 30 seconds. Add water, lather, rinse.

Inactive Ingredients

Water, Cocamidopropyl PG-Dimonium Chloride Phosphate, Cocamidopropyl Betaine, PEG-6 Cocamide, Hydroxyethyl Cellulose, Laurtrimonium Chloride, Iodopropynyl Butylcarbamate, Methylisothiazolinone.

QUESTIONS

Kutol Product Co.
Cincinnati, OH 45241
www.Kutol.com